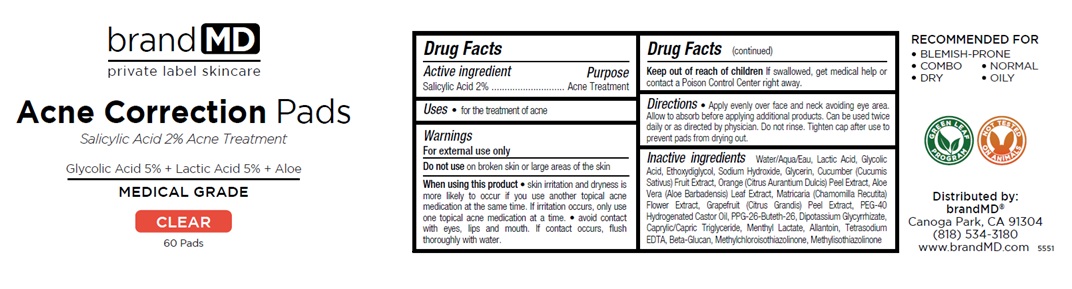 DRUG LABEL: Acne Correction Pads
NDC: 72957-012 | Form: CLOTH
Manufacturer: Private Label Skin Care
Category: otc | Type: HUMAN OTC DRUG LABEL
Date: 20250226

ACTIVE INGREDIENTS: SALICYLIC ACID 2 g/100 mL
INACTIVE INGREDIENTS: WATER; LACTIC ACID, UNSPECIFIED FORM; GLYCOLIC ACID; DIETHYLENE GLYCOL MONOETHYL ETHER; SODIUM HYDROXIDE; GLYCERIN; CUCUMBER; ORANGE PEEL; ALOE VERA LEAF; CHAMOMILE; CITRUS MAXIMA FRUIT RIND; POLYOXYL 40 HYDROGENATED CASTOR OIL; PPG-26-BUTETH-26; GLYCYRRHIZINATE DIPOTASSIUM; MEDIUM-CHAIN TRIGLYCERIDES; MENTHYL LACTATE, (-)-; ALLANTOIN; EDETATE SODIUM; 1,3-BETA-GLUCAN SYNTHASE COMPONENT FKS1; METHYLCHLOROISOTHIAZOLINONE; METHYLISOTHIAZOLINONE

Acne Correction Pads

Active ingredient

Salicylic Acid 2%

Purpose

Acne Treatment

Uses

• for the treatment of acne

Warnings

For external use only

Do not use on broken skin or large areas of the skin

When using this product • skin irritation and dryness is more likely to occur if you use another topical acne medication at the same time. If irritation occurs, only use one topical acne medication at a time. • avoid contact with eyes, lips and mouth. If contact occurs, flush thoroughly with water.

Keep out of reach of children If swallowed, get medical help or contact a Poison Control Center right away.

Directions

• Apply evenly over face and neck avoiding eye area. Allow to absorb before applying additional products. Can be used twice daily or as directed by physician. Do not rinse. Tighten cap after use to prevent pads from drying out.

Inactive ingredients

Water/Aqua/Eau, Lactic Acid, Glycolic Acid, Ethoxydiglycol, Sodium Hydroxide, Glycerin, Cucumber (Cucumis Sativus) Fruit Extract, Orange (Citrus Aurantium Dulcis) Peel Extract, Aloe Vera (Aloe Barbadensis) Leaf Extract, Matricaria (Chamomilla Recutita) Flower Extract, Grapefruit (Citrus Grandis) Peel Extract, PEG-40 Hydrogenated Castor Oil, PPG-26-Buteth-26, Dipotassium Glycyrrhizate, Caprylic/Capric Triglyceride, Menthyl Lactate, Allantoin, Tetrasodium EDTA, Beta-Glucan, Methylchloroisothiazolinone, Methylisothiazolinone

brand MD

Glycolic Acid 5% + Lactic Acid 5% + Aloe

MEDICAL GRADE

CLEAR

RECOMMENDED FOR
• BLEMISH-PRONE
• COMBO • NORMAL
• DRY • OILY

GREEN LEAF PROGRAM

NOT TESTED ON ANIMALS

Distributed by:
brandMD®
Canoga Park, CA 91304
(818) 534-3180
www.brandMD.com